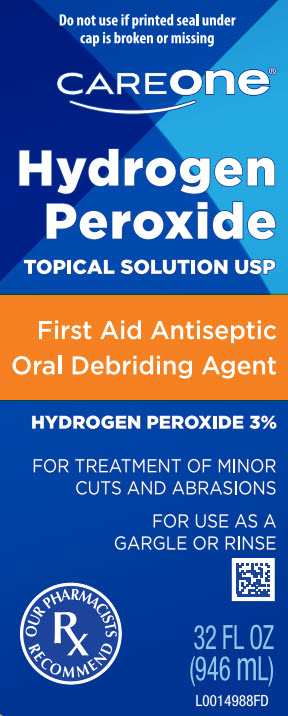 DRUG LABEL: Hydrogen Peroxide
NDC: 72476-942 | Form: SOLUTION
Manufacturer: Retail Business Services, LLC 
Category: otc | Type: HUMAN OTC DRUG LABEL
Date: 20260206

ACTIVE INGREDIENTS: HYDROGEN PEROXIDE 30 mg/1 mL
INACTIVE INGREDIENTS: WATER

Care One 871.001/871AA
3% Hydrogen Peroxide

DISTRIBUTED BY FOODHOLD U.S.A., LLC

LANDOVER, MD 20785 1-877-846-9949

(c)2016 S&S BRANDS, LLC

Quality Guaranteed or your money back

Active ingredient

Hydrogen peroxide (stabilized) 3%

Purpose

First Aid Antiseptic

Oral debriding agent

Use

- first aid to help prevent the risk of infection in minor cuts, scrapes and burns
- aids in the removal of phlegm, mucus, or other secretions associated with occasional sore mouth

Warnings

For external use only

Do not use

- in the eyes or apply over large areas of the body
- longer than 1 week

Ask a doctor before use if you have

deep or pucture wounds, animal bites or serious burns

Stop Use and ask a doctor if

- the condition persists or gets worse
- sore mouth symptoms do not improve in 7 days
- irritation, pain, or redness persists or worsens
- swelling, rash, or fever develops

Keep out of reach of children.

If swallowed, get medical help or contact a Poison Control Center right away.

Directions

First Aid Antiseptic:

- clean the affected area
- apply a small amount of the product on the affected area 1 to 3 times a day
- may be covered with a sterile bandage
- if bandage, let dry first

Oral Debriding Agent:

- adults, children over 2 years of age
- mix with equal amount of water
- swish around in the mouth over the affected area for at least 1 minute, then spit out
- use up to 4 times daily after meals and at bedtime
- children under 12 years of age should be supervised in the use
- children under 2 years of age: consult a dentist or doctor

Other information

Keep tightly closed and at controlled room temperature. Do not shake bottle. Hold away from face when opening.

Inactive ingredient

purified water

principal display panel

Do not use if printed seal under cap is broken or missing

CAREONE

Hydrogen Peroxide

TOPICAL SOLUTION USP

First Aid Antiseptic

Oral Debriding Agent

HYDROGEN PEROXIDE 3%

FOR TREATMENT OF MINOR CUTS AND ABRASIONS

FOR USE AS A GARGLE OR RINSE

OUR PHARMACISTS RECOMMENDED

32 FL OZ (946 mL)